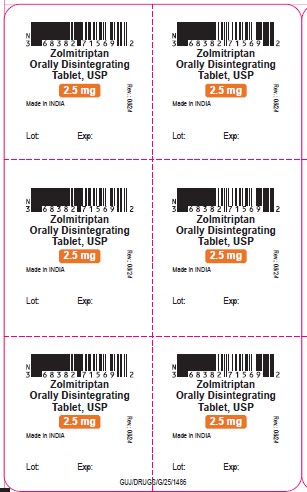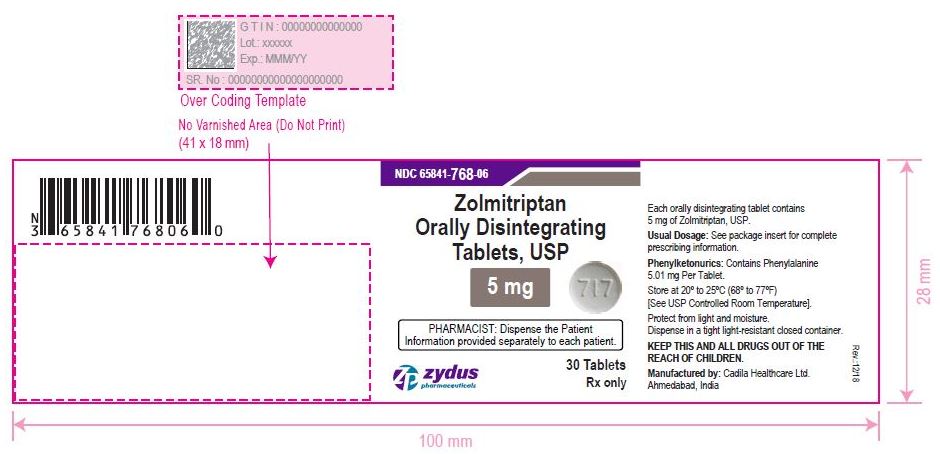 DRUG LABEL: Zolmitriptan
NDC: 65841-767 | Form: TABLET, ORALLY DISINTEGRATING
Manufacturer: Zydus Lifesciences Limited
Category: prescription | Type: HUMAN PRESCRIPTION DRUG LABEL
Date: 20240814

ACTIVE INGREDIENTS: ZOLMITRIPTAN 2.5 mg/1 1
INACTIVE INGREDIENTS: ANHYDROUS CITRIC ACID; ASPARTAME; SILICON DIOXIDE; CROSPOVIDONE (15 MPA.S AT 5%); GELATIN; MAGNESIUM STEARATE; MANNITOL; CELLULOSE, MICROCRYSTALLINE; ORANGE; POLACRILIN POTASSIUM; SODIUM STEARYL FUMARATE

ZOLMITRIPTAN ORALLY DISTRAGING TABLETS

PACKAGE LABEL

NDC 65841-767-69 in blister pack of 6 Tablets

Zolmitriptan Orally Disintegrating Tablets, 2.5 mg

Rx only

6 Tablets

PACKAGE LABEL

NDC 65841-768-87 in blister pack of 3 Tablets

Zolmitriptan Orally Disintegrating Tablets, 5 mg

Rx only

3 Tablets